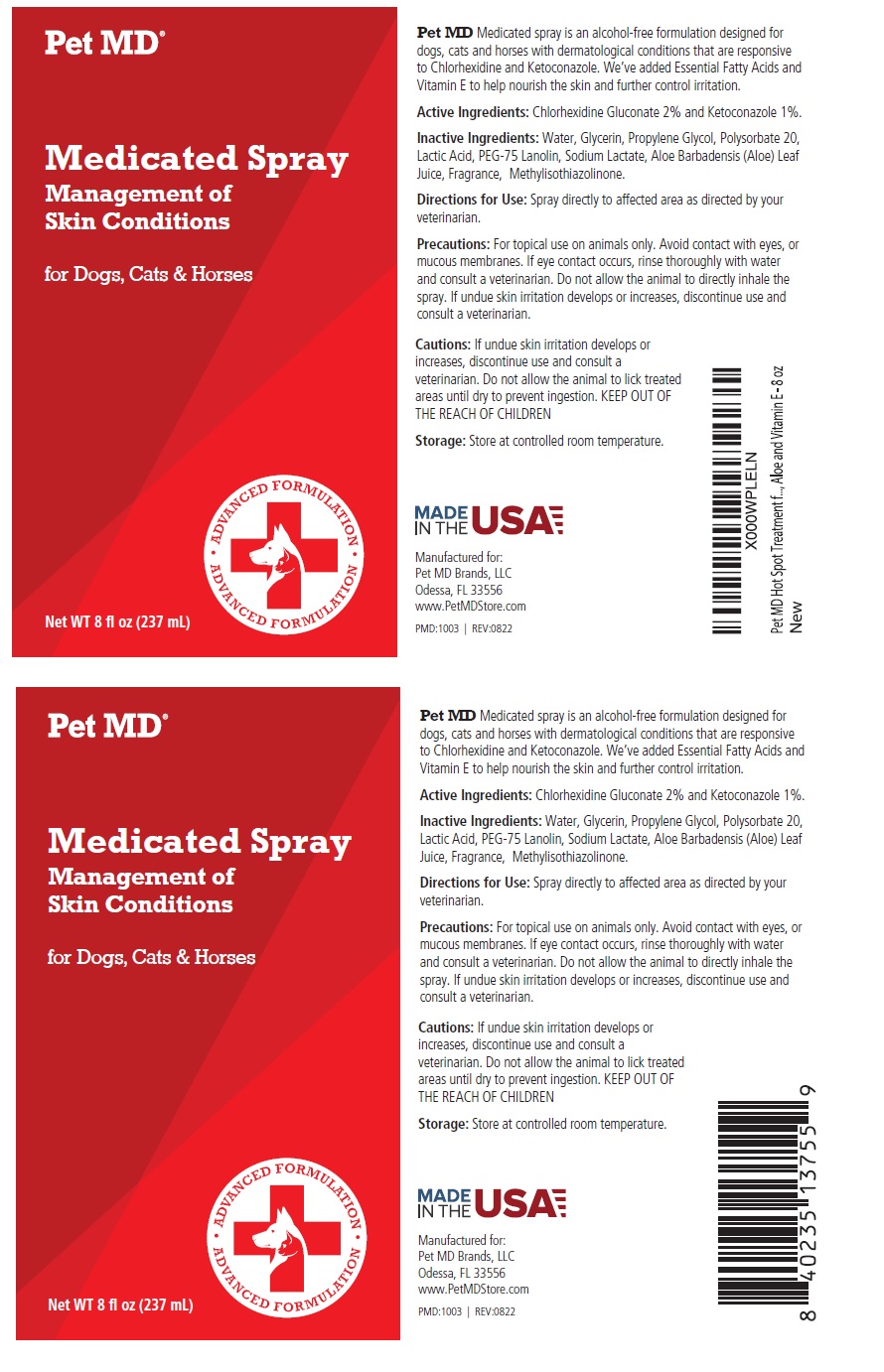 DRUG LABEL: Pet MD Medicated
NDC: 86090-007 | Form: SPRAY
Manufacturer: Pet MD Brands, LLC
Category: animal | Type: OTC ANIMAL DRUG LABEL
Date: 20230907

ACTIVE INGREDIENTS: CHLORHEXIDINE GLUCONATE 2 g/100 mL; KETOCONAZOLE 1 g/100 mL
INACTIVE INGREDIENTS: WATER; GLYCERIN; PROPYLENE GLYCOL; POLYSORBATE 20; LACTIC ACID, UNSPECIFIED FORM; PEG-75 LANOLIN; SODIUM LACTATE; ALOE VERA LEAF; METHYLISOTHIAZOLINONE

Pet MD® Medicated Spray

Active Ingredients:

Chlorhexidine Gluconate 2% and Ketoconazole 1%.

INDICATIONS AND USAGE

Pet MD Medicated spray is an alcohol-free formulation designed for dogs, cats and horses with dermatological conditions that are responsive to Chlorhexidine and Ketoconazole. We’ve added Essential Fatty Acids and Vitamin E to help nourish the skin and further control irritation.

Inactive Ingredients:

Water, Glycerin, Propylene Glycol, Polysorbate 20, Lactic Acid, PEG-75 Lanolin, Sodium Lactate, Aloe Barbadensis (Aloe) Leaf Juice, Fragrance, Methylisothiazolinone.

Directions for Use:

Spray directly to affected area as directed by your veterinarian.

Precautions:

For topical use on animals only. Avoid contact with eyes, or mucous membranes. If eye contact occurs, rinse thoroughly with water and consult a veterinarian. Do not allow the animal to directly inhale the spray.

Cautions:

If undue skin irritation develops or increases, discontinue use and consult a veterinarian. Do not allow the animal to lick treated areas until dry to prevent ingestion. KEEP OUT OF THE REACH OF CHILDREN

Storage:

Store at controlled room temperature.

Management of Skin Conditions

for Dogs, Cats & Horses

ADVANCED FORMULATION

MADE IN THE USA

Manufactured for:
Pet MD Brands, LLC
Odessa, FL 33556
www.PetMDStore.com